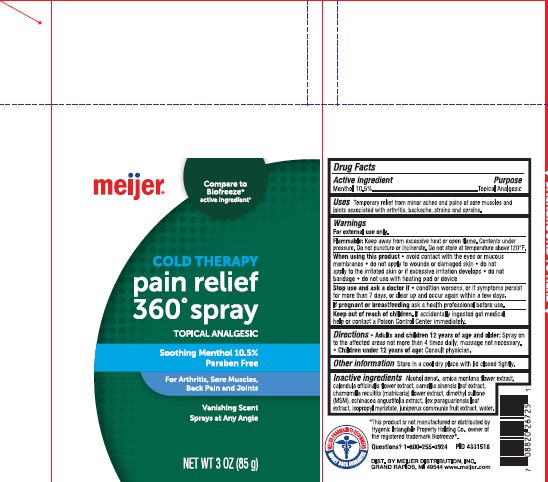 DRUG LABEL: Meijer Cold Therapy Pain Relief 360
NDC: 52313-1112 | Form: SPRAY
Manufacturer: Sklar BOV Solutions Inc
Category: otc | Type: HUMAN OTC DRUG LABEL
Date: 20220131

ACTIVE INGREDIENTS: MENTHOL 105 mg/1 g
INACTIVE INGREDIENTS: ECHINACEA, UNSPECIFIED; ARNICA MONTANA; ISOPROPYL MYRISTATE; DIMETHYL SULFONE; WATER; CALENDULA OFFICINALIS FLOWER; CHAMOMILE; JUNIPERUS COMMUNIS WHOLE; CAMELLIA SINENSIS WHOLE; ALCOHOL; ILEX PARAGUARIENSIS LEAF

Meijer Cold Therapy Pain Relief 360

Active Ingredient Purpose

Menthol 10.5% Cooling Pain Relief

Use

Temporary relief of minor aches and pains of sore muscles and joints associated with arthritis, backaches, strains and springs.

Warnings

For external use only

Flammable

Keep away from excessive heat or open flame. Contents umder pressure. Do not store at temperatures above 120ºF.

INDICATIONS AND USAGE

When using the product avoid contact with the eyes or mucous membranes.,do not apply to wounds or damaged skin, do

not apply to the irritated skin or if excessive irritation develops, do not bandage, do not use with heating pad of device.

Stop and ask a doctor if, condition worsens or if symptoms persist for more than 7 days or clear up and occur again with a few

days

If pregnant or breastfeeding, ask a health professional before use.

Keep out of reach of Children. Iff accidentally ingested get medical help of contacat a Poison Control Center immediately.

DOSAGE AND ADMINISTRATION

Directions , Adults and Children 12 yearsof age and older.

Spray on the affected areas not more that 4 times daily., massage not necessary.

Children under 12 years of age. Consult a doctor

WARNINGS AND PRECAUTIONS

Other informaton

Store in a cool dry place with lid closed tightly

Inactive Ingredients

Alcohol denat. arnica montana flower extract, calendula officinalis flower extract, camellia sinensis leaf extract, chamomillx recuitita (matricaria) flower extract, dimethyl sulfone (MSM), ecinacea angustifolia extract, ilex paraguariensis leaf extract, isopropyl myristate, juniperus communis fruit extract, water

Questions 1-800-255-3924

PACKAGE LABEL

85 grams NDC 52313-1112-1 Cold Therapy pain relief 360º

Topical Analgesis

Soothing Menthol 10.5%

Paraben Free

For Arthritus, Sore Muscles, Back Pain and Joints.

Vanishing Scent

Spray at any angle.